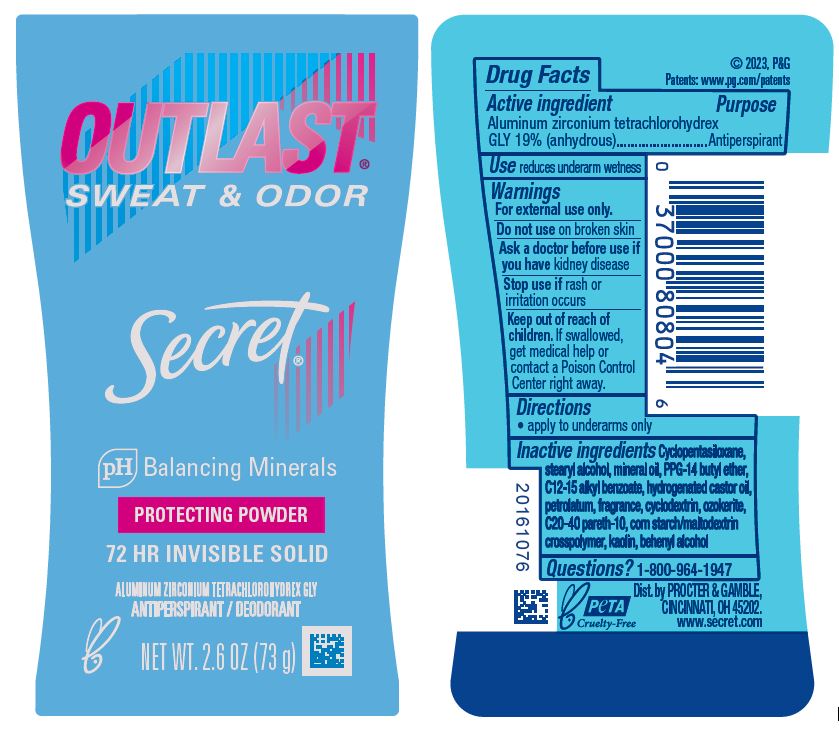 DRUG LABEL: Secret Outlast Invisible Protecting
NDC: 69423-464 | Form: STICK
Manufacturer: The Procter & Gamble Manufacturing Company
Category: otc | Type: HUMAN OTC DRUG LABEL
Date: 20251216

ACTIVE INGREDIENTS: ALUMINUM ZIRCONIUM TETRACHLOROHYDREX GLY 19 g/100 g
INACTIVE INGREDIENTS: C12-15 ALKYL BENZOATE; CYCLOPENTASILOXANE; STEARYL ALCOHOL; MINERAL OIL; KAOLIN; PETROLATUM; HYDROGENATED CASTOR OIL; PPG-14 BUTYL ETHER; C20-40 PARETH-10; BEHENYL ALCOHOL; CERESIN; CYCLODEXTRINS

Secret® Outlast™ Invisible
Protecting Powder

Drug Facts

Active ingredient

Aluminum zirconium tetrachlorohydrex Gly 19% (anhydrous)

Purpose

Antiperspirant

Use

reduces underarm wetness

Warnings

For external use only.

Do not use on broken skin

Ask a doctor before use if you have kidney disease

Stop use if rash or irritation occurs

Keep out of reach of children. If swallowed, get medical help or contact a Poison Control Center right away.

Directions

apply to underarms only

Inactive ingredients

Cyclopentasiloxane, stearyl alcohol, mineral oil, PPG-14 butyl ether, C12-15 alkyl benzoate, hydrogenated castor oil, petrolatum, fragrance, cyclodextrin, ozokerite, C20-40 pareth-10, corn starch/maltodextrin crosspolymer, kaolin, behenyl alcohol

Questions?

1-800-964-1947

Dist. by PROCTER & GAMBLE,
CINCINNATI, OH 45202.

PRINCIPAL DISPLAY PANEL - 73 g Cylinder Label

Secret®

OUTLAST™

SWEAT & ODOR

pH Balancing Minerals

PROTECTING POWDER

72 HR INVISIBLE SOLID

ALUMINUM ZIRCONIUM TETRACHLOROHYDREX GLY
ANTIPERSPIRANT / DEODORANT

NET WT. 2.6 OZ (73 g)